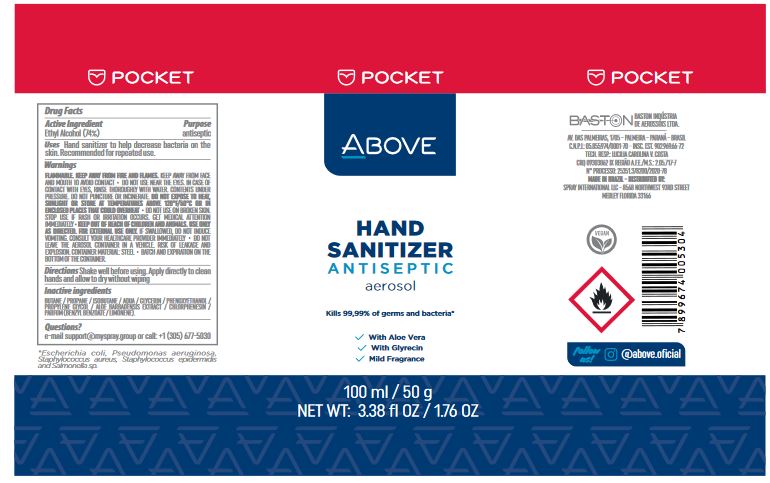 DRUG LABEL: Above Hand Sanitizer Antiseptic
NDC: 73306-6002 | Form: AEROSOL
Manufacturer: Baston Industria De Aerossols Ltda
Category: otc | Type: HUMAN OTC DRUG LABEL
Date: 20200918

ACTIVE INGREDIENTS: ALCOHOL 0.74 mL/1 g
INACTIVE INGREDIENTS: BUTANE; PROPANE; ISOBUTANE; WATER; GLYCERIN; PHENOXYETHANOL; PROPYLENE GLYCOL; ALOE VERA LEAF; CHLORPHENESIN; BENZYL BENZOATE; LIMONENE, (+)-

Above Hand Sanitizer Antiseptic Aerosol

Active Ingredient

Ethyl Alcohol (74%)

Purpose

antiseptic

Uses

Hand sanitizer to help decrease bacteria on the skin. Recommended for repeated use.

Warnings

FLAMMABLE. KEEP AWAY FROM FIRE AND FLAMES. KEEP AWAY FROM FACE AND MOUTH TO AVOID CONTACT

DO NOT USE

- NEAR THE EYES. IN CASE OF CONTACT WITH EYES, RINSE THOROUGHLY WITH WATER. CONTENTS UNDER PRESSURE. DO NOT PUNCTURE OR INCINERATE. DO NOT EXPOSE TO HEAT, SUNLIGHT OR STORE AT TEMPERATURES ABOVE 120°F/50°C OR IN ENCLOSED PLACES THAT COULD OVERHEAT
- DO NOT USE ON BROKEN SKIN.

STOP USE

IF RASH OR IRRITATION OCCURS. GET MEDICAL ATTENTION IMMEDIATELY

KEEP OUT OF REACH OF CHILDREN AND ANIMALS.

- USE ONLY AS DIRECTED. FOR EXTERNAL USE ONLY. IF SWALLOWED, DO NOT INDUCE VOMITING. CONSULT YOUR HEALTHCARE PROVIDER IMMEDIATELY
- DO NOT LEAVE THE AEROSOL CONTAINER IN A VEHICLE. RISK OF LEAKAGE AND EXPLOSION. CONTAINER MATERIAL: STEEL
- BATCH AND EXPIRATION ON THE BOTTOM OF THE CONTAINER.

Directions

Shake well before using. Apply directly to clean hands and allow to dry without wiping

Inactive ingredients

BUTANE / PROPANE / ISOBUTANE / AQUA / GLYCERIN / PHENOXYETHANOL / PROPYLENE GLYCOL / ALOE BARBADENSIS EXTRACT / CHLORPHENESIN / PARFUM (BENZYL BENZOATE / LIMONENE).

Questions?

e-mail support@myspray.group or call: +1 (305) 677-5030